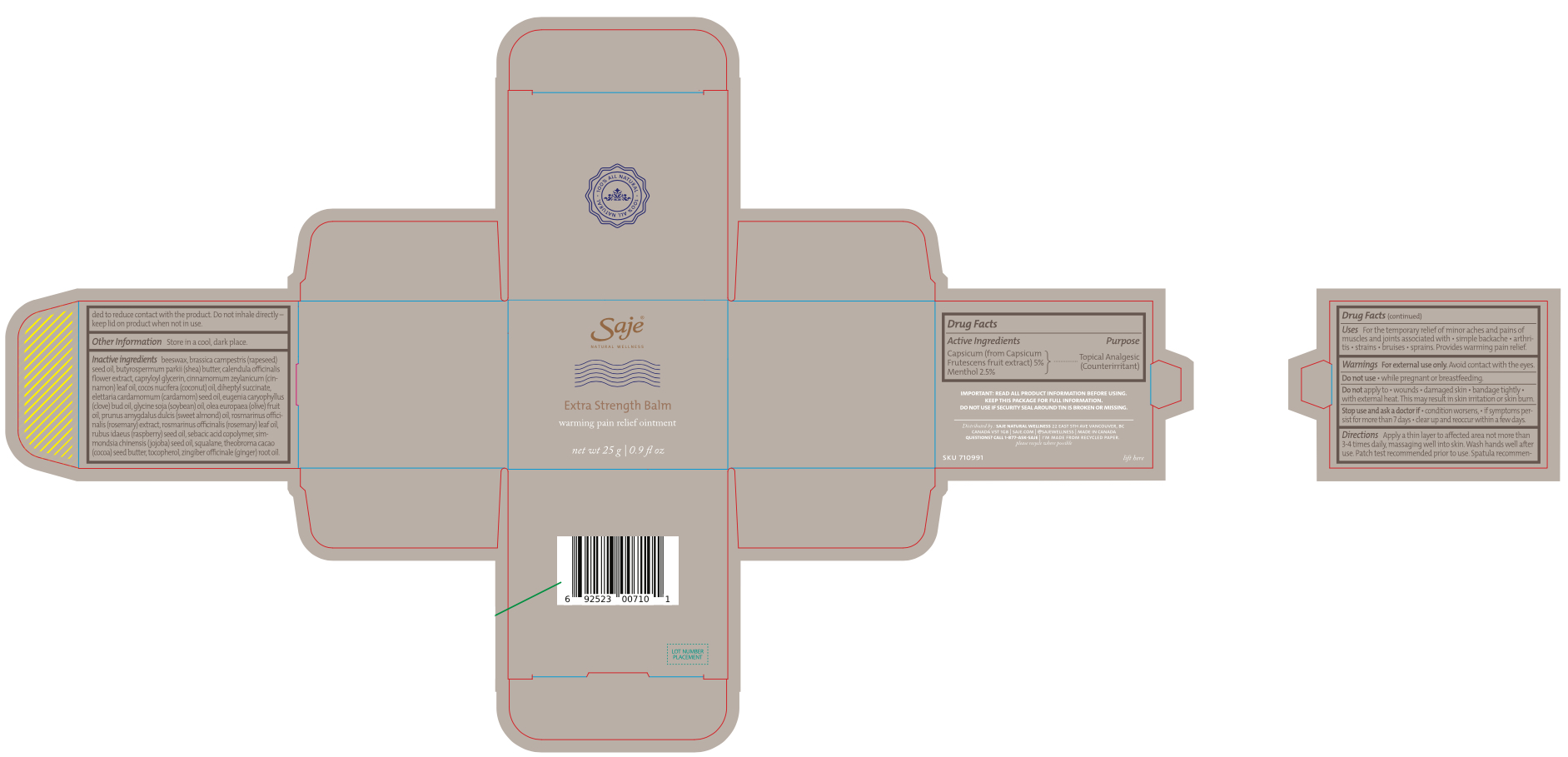 DRUG LABEL: Extra Strength Balm
NDC: 69204-030 | Form: OINTMENT
Manufacturer: NATURES FORMULAE HEALTH PRODUCTS LTD.
Category: otc | Type: HUMAN OTC DRUG LABEL
Date: 20260129

ACTIVE INGREDIENTS: CAPSICUM 5 g/100 g; MENTHOL 2.5 g/100 g
INACTIVE INGREDIENTS: ELETTARIA CARDAMOMUM SEED OIL; SIMMONDSIA CHINENSIS (JOJOBA) SEED OIL; ROSMARINUS OFFICINALIS (ROSEMARY) LEAF OIL; SQUALANE; ZINGIBER OFFICINALE (GINGER) ROOT OIL; RUBUS IDAEUS (RASPBERRY) SEED OIL; COCOS NUCIFERA (COCONUT) OIL; OLEA EUROPAEA (OLIVE) FRUIT OIL; TOCOPHEROL; CAPRYLOYL GLYCERIN/SEBACIC ACID COPOLYMER (2000 MPA.S); EUGENIA CARYOPHYLLUS (CLOVE) BUD OIL; ROSEMARY; HYDROGENATED CASTOR OIL/SEBACIC ACID COPOLYMER; THEOBROMA CACAO (COCOA) SEED BUTTER; CINNAMOMUM ZEYLANICUM LEAF OIL; CALENDULA OFFICINALIS FLOWER; BEESWAX; BRASSICA CAMPESTRIS (RAPESEED) SEED OIL; PRUNUS AMYGDALUS DULCIS (SWEET ALMOND) OIL; DIHEPTYL SUCCINATE; BUTYROSPERMUM PARKII (SHEA) BUTTER; SOYBEAN OIL

Extra Strength Balm

Active Ingredients

Capsicum (from Capsicum Frutescens fruit extract) 5%

Menthol 2.5%

Purpose

Topical Analgesic (Counterirritant)

Uses

For the temporary relief of minor aches and pains of muscles and joints associated with • simple backache • arthritis • strains • bruises • sprains. Provides warming pain relief.

Warnings

For external use only.

WHEN USING

Avoid contact with the eyes

Do not use • while pregnant or breastfeeding.

DO NOT USE

Do not apply to • wounds • damaged skin • bandage tightly • with external heat. This may result in skin irritation or skin burn.

Stop use and ask a doctor if • condition worsens, • if symptoms persist for more than 7 days • clear up and reoccur within a few days.

Keep out of reach of children. If product is swallowed, get medical help or contact a Poison Control Center right away.

Directions

Apply a thin layer to affected area not more than 3-4 times daily, massaging well into skin. Wash hands well after use. Patch test recommended prior to use. Spatula recommended to reduce contact with the product. Do not inhale directly–keep lid on product when not in use.

Other Information

Store in a cool, dry place.

Inactive Ingredients

Beeswax, butyrospermum parkii (shea) butter, calendula officinalis flower extract, capryloyl glycerin, cinnamomum zeylanicum (cinnamon) leaf oil, cocos nucifera (coconut) oil, diheptyl succinate, elettaria cardamomum (cardamom) seed oil, eugenia caryophyllus (clove) bud oil, glycine soja (soybean) oil, olea europaea (olive) fruit oil, prunus amygdalus dulcis (sweet almond) oil, rosmarinus officinalis (rosemary) extract, rosmarinus officinalis (rosemary) leaf oil, rubus idaeus (raspberry) seed oil, sebacic acid copolymer, simmondsia chinensis (jojoba) seed oil, squalane, theobroma cacao (cocoa) seed butter, tocopherol, zingiber officinale (ginger) root oil

PACKAGE LABEL

Saje

Natural Wellness

Extra Strength Balm

Warming pain relief ointment

net wt 25 g | 0.9 fl oz